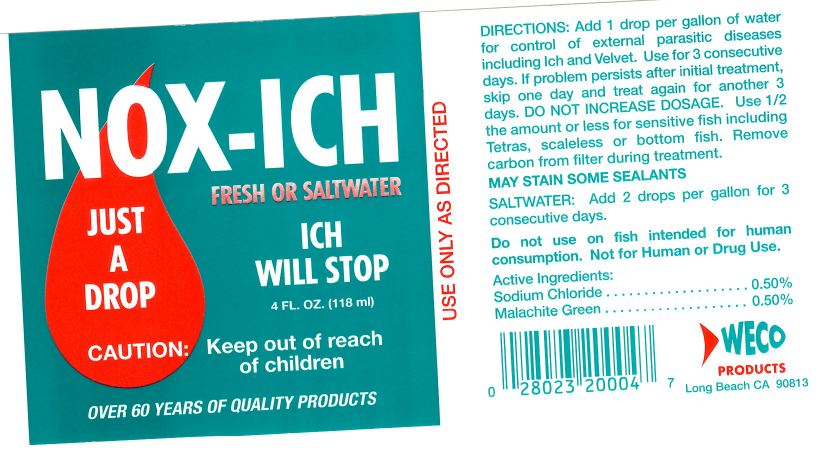 DRUG LABEL: Nox-Ich
NDC: 86027-001 | Form: SOLUTION
Manufacturer: Weco Products
Category: animal | Type: OTC ANIMAL DRUG LABEL
Date: 20140826

ACTIVE INGREDIENTS: SODIUM CHLORIDE 5 mg/1 mL; MALACHITE GREEN 5 mg/1 mL
INACTIVE INGREDIENTS: water

NOX-ICH

Directions:

Add one drop per gallon of water for control of external parasitic diseases including Ich and Velvet. Use for 3 consecutive days. If the problem persists after initial treatment, skip one day and treat again for another 3 days. DO NOT INCREASE DOSAGE. Use 1/2 the amount or less for sensitive fish including Tetras, scaleless or bottom fish. Remove carbon from filter during treatment.

WARNINGS

MAY STAIN SOME SEALANTS

SALTWATER:

Add 2 drops per gallon for 3 consecutive days.

Do not use on fish intended for human consumption. Not for Human or Drug use.

Active Ingredients:

Sodium Chloride.....................0.50%

Malachite Green......................0.50%

WARNINGS

USE ONLY AS DIRECTED